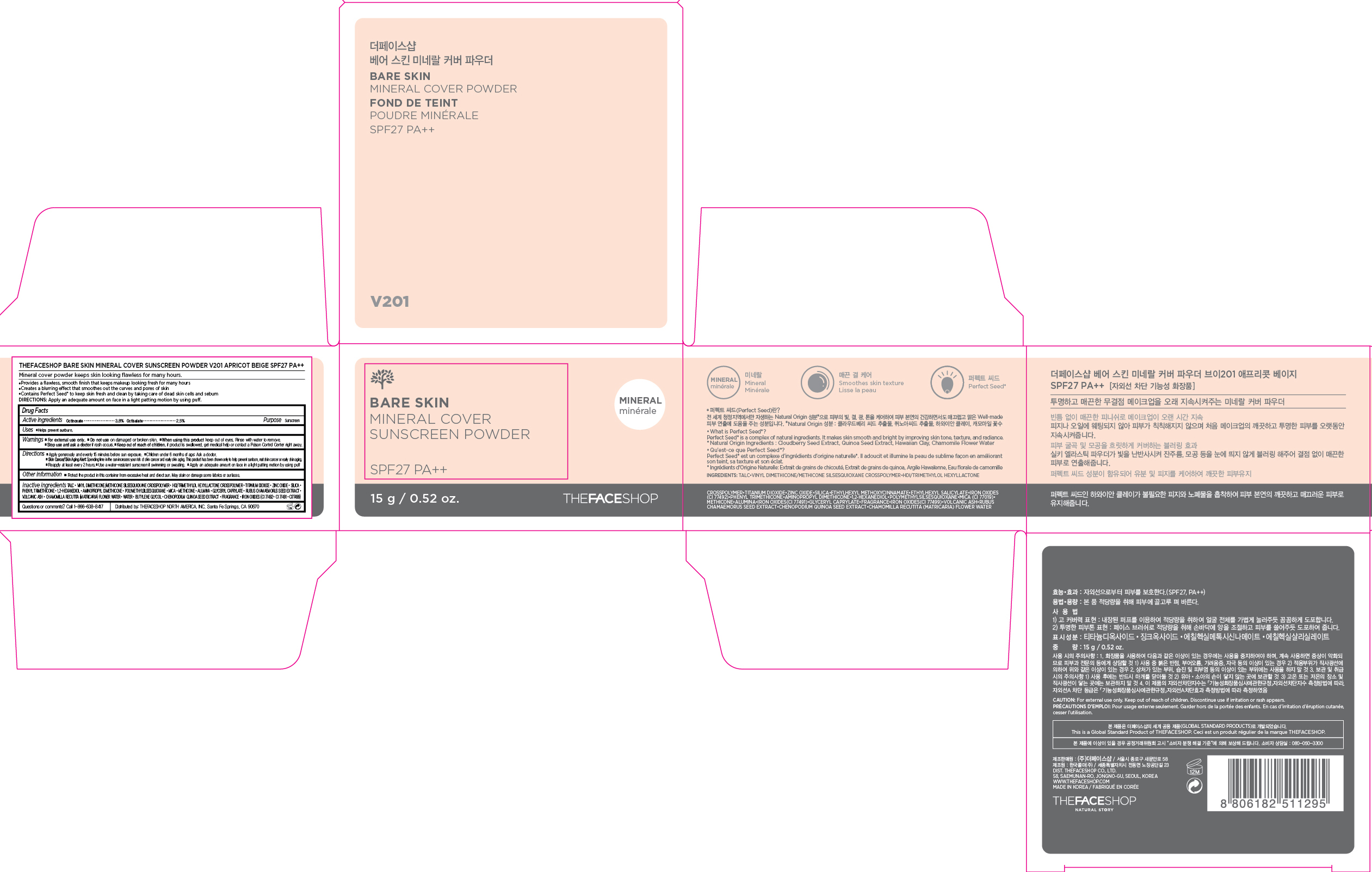 DRUG LABEL: BARE SKIN
NDC: 51523-474 | Form: POWDER
Manufacturer: THEFACESHOP CO., LTD.
Category: otc | Type: HUMAN OTC DRUG LABEL
Date: 20150929

ACTIVE INGREDIENTS: OCTINOXATE 0.57 g/15 g; OCTISALATE 0.38 g/15 g
INACTIVE INGREDIENTS: WATER

BARE SKIN MINERAL COVER SUNSCREEN POWDER SPF27 PA++ 34200474

Active Ingredients

Octinoxate 3.8 %

Octisalate 2.5 %

Purpose

Sunscreen

Sunscreen

Uses:

Helps prevent sunburn.

Warnings

For external use only.

Do not use on damaged or broken skin

When using this product keep out of eyes. Rinse with water to remove.

Stop use and ask a doctor if rash occurs.

Keep out of reach of children. If product is swallowed, get medical help or contact a Poison Control Center right away.

Directions

Apply generously and evenly 15 minutes before sun exposure.
Children under 6 months of age: Ask a doctor.
Skin Cancer/Skin Aging Alert: Spending time in the sun increases your risk of skin cancer and early skin aging. This product has been shown only to help prevent sunburn, not skin cancer or early skin aging.
Reapply at least every 2 hours.
Use a water-resistant sunscreen if swimming or sweating.

Apply an adequate amount on face in a light patting motion by using puff.

OTHER SAFETY INFORMATION

Protect the product in this container from excessive heat and direct sun.

May stain or damage some fabrics or surfaces.

Inactive Ingredients:

TALC, VINYL DIMETHICONE/METHICONE SILSESQUIOXANE CROSSPOLYMER, HDI/TRIMETHYLOL HEXYLLACTONE CROSSPOLYMER, TITANIUM DIOXIDE, ZINC OXIDE, SILICA, PHENYL TRIMETHICONE, 1,2-HEXANEDIOL, AMINOPROPYL DIMETHICONE, POLYMETHYLSILSESQUIOXANE, MICA, METHICONE, ALUMINA, GLYCERYL CAPRYLATE, RUBUS CHAMAEMORUS SEED EXTRACT,VOLCANIC ASH, CHAMOMILLA RECUTITA (MATRICARIA) FLOWER WATER, WATER, BUTYLENE GLYCOL, CHENOPODIUM QUINOA SEED EXTRACT

Questions or comments? Call 1-866-638-8417

Distributed by:

THEFACESHOP NORTH AMERICA, INC.

Santa Fe Springs, CA 90670

PACKAGE LABEL

BARE SKIN
MINERAL COVER SUNSCREEN POWDER
V201 APRICOT BEIGE SPF27 PA++
Mineral cover powder keeps skin looking flawless for many hours.
Provides a flawless, smooth finish that keeps makeup looking fresh for may hours.
Creates a blurring effect that smoothes out the curves and pores of the skin.
Contains Perfect Seed to keep skin fresh and clean by taking care of dead skin cells and sebum.